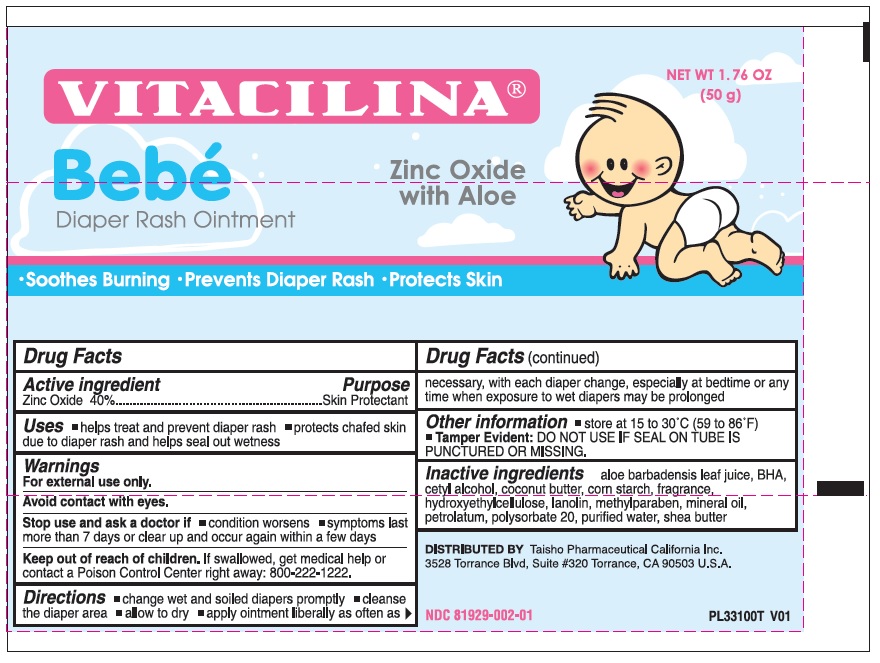 DRUG LABEL: Vitacilina Bebe Diaper Rash
NDC: 81929-002 | Form: OINTMENT
Manufacturer: Taisho Pharmaceutical California Inc.
Category: otc | Type: HUMAN OTC DRUG LABEL
Date: 20250807

ACTIVE INGREDIENTS: ZINC OXIDE 400 mg/1 g
INACTIVE INGREDIENTS: ALOE VERA LEAF; BUTYLATED HYDROXYANISOLE; CETYL ALCOHOL; STARCH, CORN; HYDROXYETHYL CELLULOSE, UNSPECIFIED; LANOLIN; METHYLPARABEN; MINERAL OIL; PETROLATUM; POLYSORBATE 20; WATER; SHEA BUTTER

Vitacilina Bebe Diaper Rash Ointment

Active ingredient

Zinc Oxide 40%

Purpose

Skin Protectant

Uses

- helps treat and prevent diaper rash
- protect chafed skin due to diaper rash and helps seal out wetness

Warnings

For external use only.

Avoid contact with eyes.

Stop use and ask a doctor if

- condition worsens
- symptoms last more than 7 days or clear up and occur again within a few days

Keep out of reach of children.

If swallowed, get medical help or contact a Poison Control Center right away: 800-222-1222.

Directions

- change wet and soiled diapers promptly
- cleanse the diaper area
- allow to dry
- apply ointment liberally as often as necessary, with each diaper change, especially at bedtime or any time when exposure to wet diapers may be prolonged

Other information

- store at 15 to 30°C (59 to 86°F)
- DO NOT USE IF SEAL ON TUBE IS PUNCTURED OR MISSING. Tamper Evident:

Inactive ingredients

paccohol, coconut butter, corn starch, fragrance, hydroxyethylcellulose, lanolin, methylparaben, mineral oil, petrolatum, polysorbate 20, purified water, shea butter